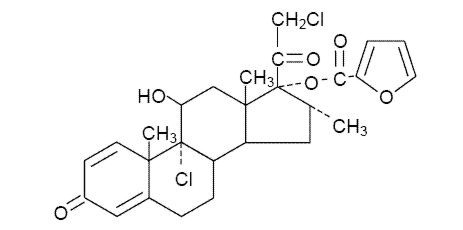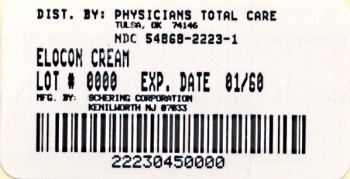 DRUG LABEL: Elocon
NDC: 54868-2223 | Form: CREAM
Manufacturer: Physicians Total Care, Inc.
Category: prescription | Type: HUMAN PRESCRIPTION DRUG LABEL
Date: 20100831

ACTIVE INGREDIENTS: MOMETASONE FUROATE 1 mg/1 g
INACTIVE INGREDIENTS: HEXYLENE GLYCOL; PHOSPHORIC ACID; PROPYLENE GLYCOL MONOSTEARATE; WHITE WAX; PETROLATUM; WATER

For Dermatologic Use Only
Not for Ophthalmic Use

PRODUCT INFORMATION

DESCRIPTION

ELOCON® (mometasone furoate cream) Cream 0.1% contains mometasone furoate, USP for dermatologic use. Mometasone furoate is a synthetic corticosteroid with anti-inflammatory activity.

Chemically, mometasone furoate is 9α,21-Dichloro-11β,17-dihydroxy-16α-methylpregna-1,4-diene-3,20-dione 17-(2-furoate), with the empirical formula C27H30Cl2O6, a molecular weight of 521.4 and the following structural formula:

Mometasone furoate is a white to off-white powder practically insoluble in water, slightly soluble in octanol, and moderately soluble in ethyl alcohol.

Each gram of ELOCON Cream 0.1% contains: 1 mg mometasone furoate, USP in a cream base of hexylene glycol, phosphoric acid, propylene glycol stearate (55% monoester), stearyl alcohol and ceteareth-20, titanium dioxide, aluminum starch octenylsuccinate (Gamma Irradiated), white wax, white petrolatum, and purified water.

CLINICAL PHARMACOLOGY

Like other topical corticosteroids, mometasone furoate has anti-inflammatory, antipruritic, and vasoconstrictive properties. The mechanism of the anti-inflammatory activity of the topical steroids, in general, is unclear. However, corticosteroids are thought to act by the induction of phospholipase A2 inhibitory proteins, collectively called lipocortins. It is postulated that these proteins control the biosynthesis of potent mediators of inflammation such as prostaglandins and leukotrienes by inhibiting the release of their common precursor arachidonic acid. Arachidonic acid is released from membrane phospholipids by phospholipase A2.

Pharmacokinetics

The extent of percutaneous absorption of topical corticosteroids is determined by many factors including the vehicle and the integrity of the epidermal barrier. Occlusive dressings with hydrocortisone for up to 24 hours have not been demonstrated to increase penetration; however, occlusion of hydrocortisone for 96 hours markedly enhances penetration. Studies in humans indicate that approximately 0.4% of the applied dose of ELOCON Cream 0.1% enters the circulation after 8 hours of contact on normal skin without occlusion. Inflammation and/or other disease processes in the skin may increase percutaneous absorption.

Studies performed with ELOCON Cream 0.1% indicate that it is in the medium range of potency as compared with other topical corticosteroids.

In a study evaluating the effects of mometasone furoate cream on the hypothalamic-pituitary-adrenal (HPA) axis, 15 grams were applied twice daily for 7 days to six adult patients with psoriasis or atopic dermatitis. The cream was applied without occlusion to at least 30% of the body surface. The results show that the drug caused a slight lowering of adrenal corticosteroid secretion.

In a pediatric trial, 24 atopic dermatitis patients, of which 19 patients were age 2 to 12 years, were treated with ELOCON Cream 0.1% once daily. The majority of patients cleared within 3 weeks.

Ninety-seven pediatric patients ages 6 to 23 months, with atopic dermatitis, were enrolled in an open-label, hypothalamic-pituitary-adrenal (HPA) axis safety study. ELOCON Cream 0.1% was applied once daily for approximately 3 weeks over a mean body surface area of 41% (range 15% to 94%). In approximately 16% of patients who showed normal adrenal function by Cortrosyn test before starting treatment, adrenal suppression was observed at the end of treatment with ELOCON Cream 0.1%. The criteria for suppression were: basal cortisol level of less than or equal to 5 mcg/dL, 30-minute post-stimulation level of less than or equal to 18 mcg/dL, or an increase of less than 7 mcg/dL. Follow-up testing 2 to 4 weeks after stopping treatment, available for 5 of the patients, demonstrated suppressed HPA axis function in one patient, using these same criteria.

INDICATIONS AND USAGE

ELOCON Cream 0.1% is a medium potency corticosteroid indicated for the relief of the inflammatory and pruritic manifestations of corticosteroid-responsive dermatoses.

ELOCON (mometasone furoate cream) Cream 0.1% may be used in pediatric patients 2 years of age or older, although the safety and efficacy of drug use for longer than 3 weeks have not been established (see PRECAUTIONS – Pediatric Use section). Since safety and efficacy of ELOCON Cream 0.1% have not been established in pediatric patients below 2 years of age, its use in this age group is not recommended.

CONTRAINDICATIONS

ELOCON Cream 0.1% is contraindicated in those patients with a history of hypersensitivity to any of the components in the preparation.

PRECAUTIONS

General

Systemic absorption of topical corticosteroids can produce reversible hypothalamic-pituitary-adrenal (HPA) axis suppression with the potential for glucocorticosteroid insufficiency after withdrawal of treatment. Manifestations of Cushing's syndrome, hyperglycemia, and glucosuria can also be produced in some patients by systemic absorption of topical corticosteroids while on treatment.

Patients applying a topical steroid to a large surface area or to areas under occlusion should be evaluated periodically for evidence of HPA axis suppression. This may be done by using the ACTH stimulation, A.M. plasma cortisol, and urinary free cortisol tests.

In a study evaluating the effects of mometasone furoate cream on the hypothalamic-pituitary-adrenal (HPA) axis, 15 grams were applied twice daily for 7 days to six adult patients with psoriasis or atopic dermatitis. The cream was applied without occlusion to at least 30% of the body surface. The results show that the drug caused a slight lowering of adrenal corticosteroid secretion.

If HPA axis suppression is noted, an attempt should be made to withdraw the drug, to reduce the frequency of application, or to substitute a less potent corticosteroid. Recovery of HPA axis function is generally prompt upon discontinuation of topical corticosteroids. Infrequently, signs and symptoms of glucocorticosteroid insufficiency may occur requiring supplemental systemic corticosteroids. For information on systemic supplementation, see Prescribing Information for those products.

Pediatric patients may be more susceptible to systemic toxicity from equivalent doses due to their larger skin surface to body mass ratios (see PRECAUTIONS—Pediatric Use).

If irritation develops, ELOCON Cream 0.1% should be discontinued and appropriate therapy instituted. Allergic contact dermatitis with corticosteroids is usually diagnosed by observing a failure to heal rather than noting a clinical exacerbation as with most topical products not containing corticosteroids. Such an observation should be corroborated with appropriate diagnostic patch testing.

If concomitant skin infections are present or develop, an appropriate antifungal or antibacterial agent should be used. If a favorable response does not occur promptly, use of ELOCON Cream 0.1% should be discontinued until the infection has been adequately controlled.

Information for Patients

Patients using topical corticosteroids should receive the following information and instructions:

1. This medication is to be used as directed by the physician. It is for external use only. Avoid contact with the eyes.
2. This medication should not be used for any disorder other than that for which it was prescribed.
3. The treated skin area should not be bandaged or otherwise covered or wrapped so as to be occlusive, unless directed by the physician.
4. Patients should report to their physician any signs of local adverse reactions.
5. Parents of pediatric patients should be advised not to use ELOCON Cream 0.1% in the treatment of diaper dermatitis. ELOCON Cream 0.1% should not be applied in the diaper area as diapers or plastic pants may constitute occlusive dressing (see DOSAGE AND ADMINISTRATION).
6. This medication should not be used on the face, underarms, or groin areas unless directed by the physician.
7. As with other corticosteroids, therapy should be discontinued when control is achieved. If no improvement is seen within 2 weeks, contact the physician.
8. Other corticosteroid-containing products should not be used with ELOCON Cream 0.1% without first consulting with the physician.

Laboratory Tests

The following tests may be helpful in evaluating patients for HPA axis suppression:

ACTH stimulation test A.M. plasma cortisol test Urinary free cortisol test Carcinogenesis, Mutagenesis, Impairment of Fertility

Long-term animal studies have not been performed to evaluate the carcinogenic potential of ELOCON (mometasone furoate cream) Cream 0.1%. Long-term carcinogenicity studies of mometasone furoate were conducted by the inhalation route in rats and mice. In a 2-year carcinogenicity study in Sprague-Dawley rats, mometasone furoate demonstrated no statistically significant increase of tumors at inhalation doses up to 67 mcg/kg (approximately 0.04 times the estimated maximum clinical topical dose from ELOCON Cream 0.1% on a mcg/m^2 basis). In a 19-month carcinogenicity study in Swiss CD-1 mice, mometasone furoate demonstrated no statistically significant increase in the incidence of tumors at inhalation doses up to 160 mcg/kg (approximately 0.05 times the estimated maximum clinical topical dose from ELOCON Cream 0.1% on a mcg/m^2 basis).

Mometasone furoate increased chromosomal aberrations in an in vitro Chinese hamster ovary cell assay, but did not increase chromosomal aberrations in an in vitro Chinese hamster lung cell assay. Mometasone furoate was not mutagenic in the Ames test or mouse lymphoma assay, and was not clastogenic in an in vivo mouse micronucleus assay, a rat bone marrow chromosomal aberration assay, or a mouse male germ-cell chromosomal aberration assay. Mometasone furoate also did not induce unscheduled DNA synthesis in vivo in rat hepatocytes.

In reproductive studies in rats, impairment of fertility was not produced in male or female rats by subcutaneous doses up to 15 mcg/kg (approximately 0.01 times the estimated maximum clinical topical dose from ELOCON Cream 0.1% on a mcg/m^2 basis).

Pregnancy Teratogenic Effects Pregnancy Category C

Corticosteroids have been shown to be teratogenic in laboratory animals when administered systemically at relatively low dosage levels. Some corticosteroids have been shown to be teratogenic after dermal application in laboratory animals.

When administered to pregnant rats, rabbits, and mice, mometasone furoate increased fetal malformations. The doses that produced malformations also decreased fetal growth, as measured by lower fetal weights and/or delayed ossification. Mometasone furoate also caused dystocia and related complications when administered to rats during the end of pregnancy.

In mice, mometasone furoate caused cleft palate at subcutaneous doses of 60 mcg/kg and above. Fetal survival was reduced at 180 mcg/kg. No toxicity was observed at 20 mcg/kg. (Doses of 20, 60, and 180 mcg/kg in the mouse are approximately 0.01, 0.02, and 0.05 times the estimated maximum clinical topical dose from ELOCON Cream 0.1% on a mcg/m^2 basis.)

In rats, mometasone furoate produced umbilical hernias at topical doses of 600 mcg/kg and above. A dose of 300 mcg/kg produced delays in ossification, but no malformations. (Doses of 300 and 600 mcg/kg in the rat are approximately 0.2 and 0.4 times the estimated maximum clinical topical dose from ELOCON Cream 0.1% on a mcg/m^2 basis.)

In rabbits, mometasone furoate caused multiple malformations (eg, flexed front paws, gallbladder agenesis, umbilical hernia, hydrocephaly) at topical doses of 150 mcg/kg and above (approximately 0.2 times the estimated maximum clinical topical dose from ELOCON Cream 0.1% on a mcg/m^2 basis). In an oral study, mometasone furoate increased resorptions and caused cleft palate and/or head malformations (hydrocephaly and domed head) at 700 mcg/kg. At 2800 mcg/kg most litters were aborted or resorbed. No toxicity was observed at 140 mcg/kg. (Doses at 140, 700, and 2800 mcg/kg in the rabbit are approximately 0.2, 0.9, and 3.6 times the estimated maximum clinical topical dose from ELOCON Cream 0.1% on a mcg/m^2 basis.)

When rats received subcutaneous doses of mometasone furoate throughout pregnancy or during the later stages of pregnancy, 15 mcg/kg caused prolonged and difficult labor and reduced the number of live births, birth weight, and early pup survival. Similar effects were not observed at 7.5 mcg/kg. (Doses of 7.5 and 15 mcg/kg in the rat are approximately 0.005 and 0.01 times the estimated maximum clinical topical dose from ELOCON Cream 0.1% on a mcg/m^2 basis.)

There are no adequate and well-controlled studies of teratogenic effects from topically applied corticosteroids in pregnant women. Therefore, topical corticosteroids should be used during pregnancy only if the potential benefit justifies the potential risk to the fetus.

Nursing Mothers

Systemically administered corticosteroids appear in human milk and could suppress growth, interfere with endogenous corticosteroid production, or cause other untoward effects. It is not known whether topical administration of corticosteroids could result in sufficient systemic absorption to produce detectable quantities in human milk. Because many drugs are excreted in human milk, caution should be exercised when ELOCON Cream 0.1% is administered to a nursing woman.

Pediatric Use

ELOCON Cream 0.1% may be used with caution in pediatric patients 2 years of age or older, although the safety and efficacy of drug use for longer than 3 weeks have not been established. Use of ELOCON Cream 0.1% is supported by results from adequate and well-controlled studies in pediatric patients with corticosteroid-responsive dermatoses. Since safety and efficacy of ELOCON Cream 0.1% have not been established in pediatric patients below 2 years of age, its use in this age group is not recommended.

ELOCON Cream 0.1% caused HPA axis suppression in approximately 16% of pediatric patients ages 6 to 23 months, who showed normal adrenal function by Cortrosyn test before starting treatment, and were treated for approximately 3 weeks over a mean body surface area of 41% (range 15% to 94%). The criteria for suppression were: basal cortisol level of less than or equal to 5 mcg/dL, 30-minute post-stimulation level of less than or equal to 18 mcg/dL, or an increase of less than 7 mcg/dL. Follow-up testing 2 to 4 weeks after study completion, available for 5 of the patients, demonstrated suppressed HPA axis function in one patient, using these same criteria. Long-term use of topical corticosteroids has not been studied in this population (see CLINICAL PHARMACOLOGY – Pharmacokinetics section).

Because of a higher ratio of skin surface area to body mass, pediatric patients are at a greater risk than adults of HPA axis suppression and Cushing's syndrome when they are treated with topical corticosteroids. They are, therefore, also at greater risk of adrenal insufficiency during and/or after withdrawal of treatment. Pediatric patients may be more susceptible than adults to skin atrophy, including striae, when they are treated with topical corticosteroids. Pediatric patients applying topical corticosteroids to greater than 20% of body surface are at higher risk of HPA axis suppression.

HPA axis suppression, Cushing's syndrome, linear growth retardation, delayed weight gain, and intracranial hypertension have been reported in pediatric patients receiving topical corticosteroids. Manifestations of adrenal suppression in children include low plasma cortisol levels, and an absence of response to ACTH stimulation. Manifestations of intracranial hypertension include bulging fontanelles, headaches, and bilateral papilledema.

ELOCON (mometasone furoate cream) Cream 0.1% should not be used in the treatment of diaper dermatitis.

Geriatric Use

Clinical studies of ELOCON Cream 0.1% included 190 subjects who were 65 years of age and over and 39 subjects who were 75 years of age and over. No overall differences in safety or effectiveness were observed between these subjects and younger subjects, and other reported clinical experience has not identified differences in responses between the elderly and younger patients. However, greater sensitivity of some older individuals cannot be ruled out.

OVERDOSAGE

Topically applied ELOCON Cream 0.1% can be absorbed in sufficient amounts to produce systemic effects (see PRECAUTIONS section).

DOSAGE AND ADMINISTRATION

Apply a thin film of ELOCON Cream 0.1% to the affected skin areas once daily. ELOCON Cream 0.1% may be used in pediatric patients 2 years of age or older. Since safety and efficacy of ELOCON Cream 0.1% have not been adequately established in pediatric patients below 2 years of age, its use in this age group is not recommended (see PRECAUTIONS – Pediatric Use section).

As with other corticosteroids, therapy should be discontinued when control is achieved. If no improvement is seen within 2 weeks, reassessment of diagnosis may be necessary. Safety and efficacy of ELOCON Cream 0.1% in pediatric patients for more than 3 weeks of use have not been established.

ELOCON Cream 0.1% should not be used with occlusive dressings unless directed by a physician. ELOCON Cream 0.1% should not be applied in the diaper area if the child still requires diapers or plastic pants as these garments may constitute occlusive dressing.

HOW SUPPLIED

ELOCON Cream 0.1% is supplied in:

15-g (NDC 54868-2223-0) tubes; boxes of one.

45-g (NDC 54868-2223-1) tubes; boxes of one.

Store at 25°C (77°F); excursions permitted to 15–30°C (59–86°F) [see USP Controlled Room Temperature]

Schering Corporation
Kenilworth, NJ 07033 USA

Rev. 3/04
18724340T
B-28070500
Copyright © 1987, 2003, Schering Corporation. All rights reserved.

Relabeling of "Additional" barcode label by:
Physicians Total Care, Inc.
Tulsa, OK 74146

PRINCIPAL DISPLAY PANEL

ELOCON Cream 0.1%